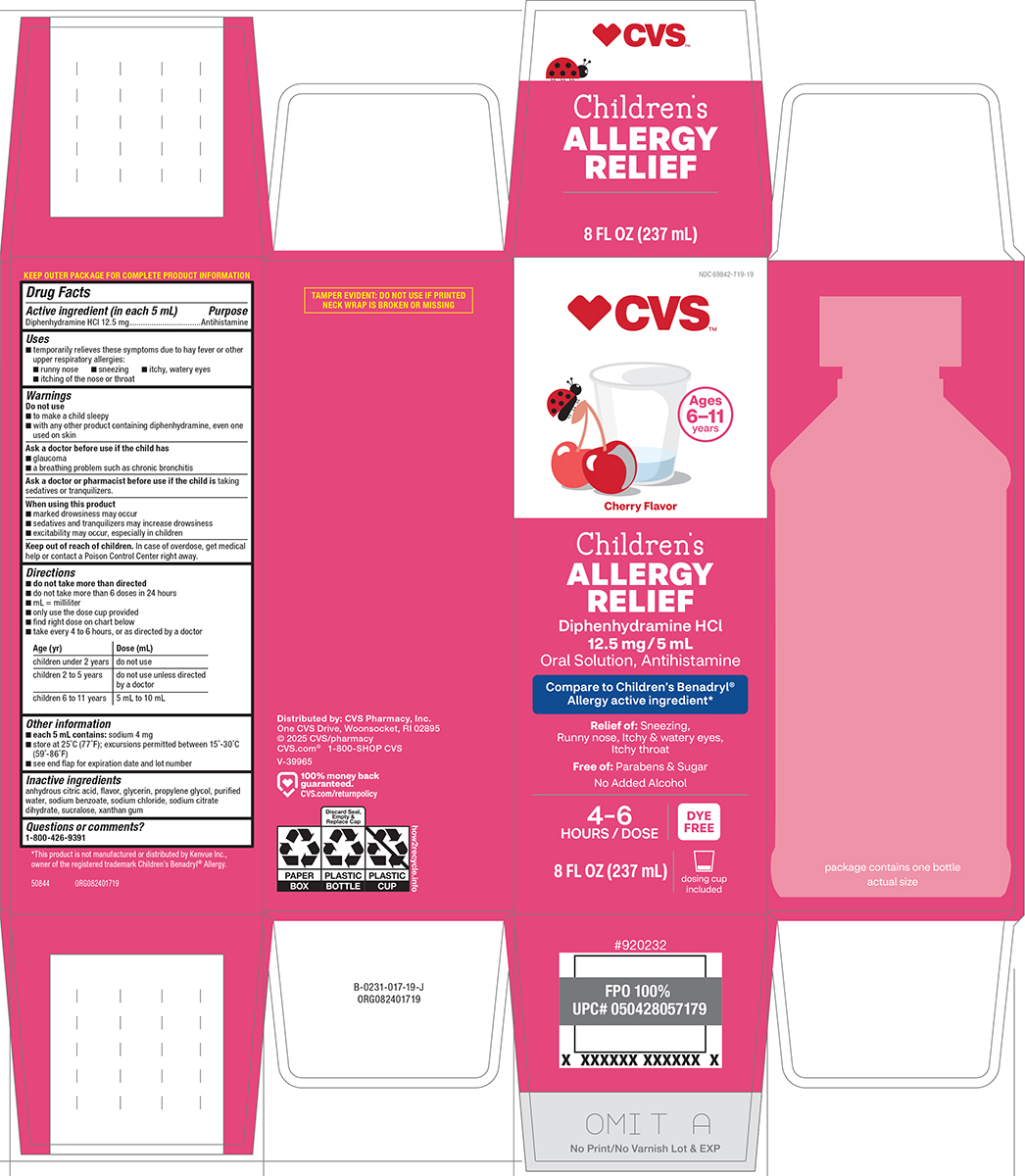 DRUG LABEL: Childrens Allergy Relief
NDC: 69842-719 | Form: SOLUTION
Manufacturer: CVS PHARMACY
Category: otc | Type: HUMAN OTC DRUG LABEL
Date: 20260112

ACTIVE INGREDIENTS: DIPHENHYDRAMINE HYDROCHLORIDE 12.5 mg/5 mL
INACTIVE INGREDIENTS: ANHYDROUS CITRIC ACID; GLYCERIN; PROPYLENE GLYCOL; WATER; SODIUM BENZOATE; SODIUM CHLORIDE; TRISODIUM CITRATE DIHYDRATE; SUCRALOSE; XANTHAN GUM

CVS 44-017

Active ingredient (in each 5 mL)

Diphenhydramine HCl 12.5 mg

Purpose

Antihistamine

Uses

- temporarily relieves these symptoms due to hay fever or other upper respiratory allergies:
  - runny nose
  - sneezing
  - itchy, watery eyes
  - itching of the nose or throat

Warnings

Do not use

- to make a child sleepy
- with any other product containing diphenhydramine, even one used on skin

Ask a doctor before use if the child has

- a breathing problem such as chronic bronchitis
- glaucoma

Ask a doctor or pharmacist before use if the child is

taking sedatives or tranquilizers.

When using this product

- marked drowsiness may occur
- sedatives and tranquilizers may increase drowsiness
- excitability may occur, especially in children

Keep out of reach of children.

In case of overdose, get medical help or contact a Poison Control Center right away.

Directions

- do not take more than directed
- do not take more than 6 doses in 24 hours
- mL = milliliter
- only use the dose cup provided
- find right dose on chart below
- take every 4 to 6 hours, or as directed by a doctor

Age (yr) | Dose (mL)
children under 2 years | do not use
children 2 to 5 years | do not use unless directed by a doctor
children 6 to 11 years | 5 mL to 10 mL

Other information

- each 5 mL contains: sodium 4 mg
- store at 25°C (77°F); excursions permitted between 15°-30°C (59°-86°F)
- see end flap for expiration date and lot number

Inactive ingredients

anhydrous citric acid, flavor, glycerin, propylene glycol, purified water, sodium benzoate, sodium chloride, sodium citrate dihydrate, sucralose, xanthan gum

Questions or comments?

1-800-426-9391

Principal display panel

♥CVS™

Ages
6-11
years
Cherry Flavor

Children’s
Allergy
Relief

Diphenhydramine HCl
12.5 mg / 5 mL
Oral Solution, Antihistamine

Relief of: Sneezing,
Runny nose, Itchy & watery eyes,
Itchy throat

Free of: Parabens & Sugar
No Added Alcohol

4–6
HOURS / DOSE

DYE
FREE

8 FL OZ (237 mL)

dosing cup
included

TAMPER EVIDENT: DO NOT USE IF PRINTED
NECK WRAP IS BROKEN OR MISSING

Package Contains
One Bottle

Actual Size

Distributed by: CVS Pharmacy, Inc.
One CVS Drive, Woonsocket, RI 02895
© 2025 CVS/pharmacy
CVS.com® 1-800-SHOP CVS
V-39965

100% money back
guaranteed.
CVS.com/returnpolicy

*This product is not manufactured or distributed by Kenvue Inc.,
owner of the registered trademark Children’s Benadryl® Allergy.

50844 ORG082401719

CVS 44-017